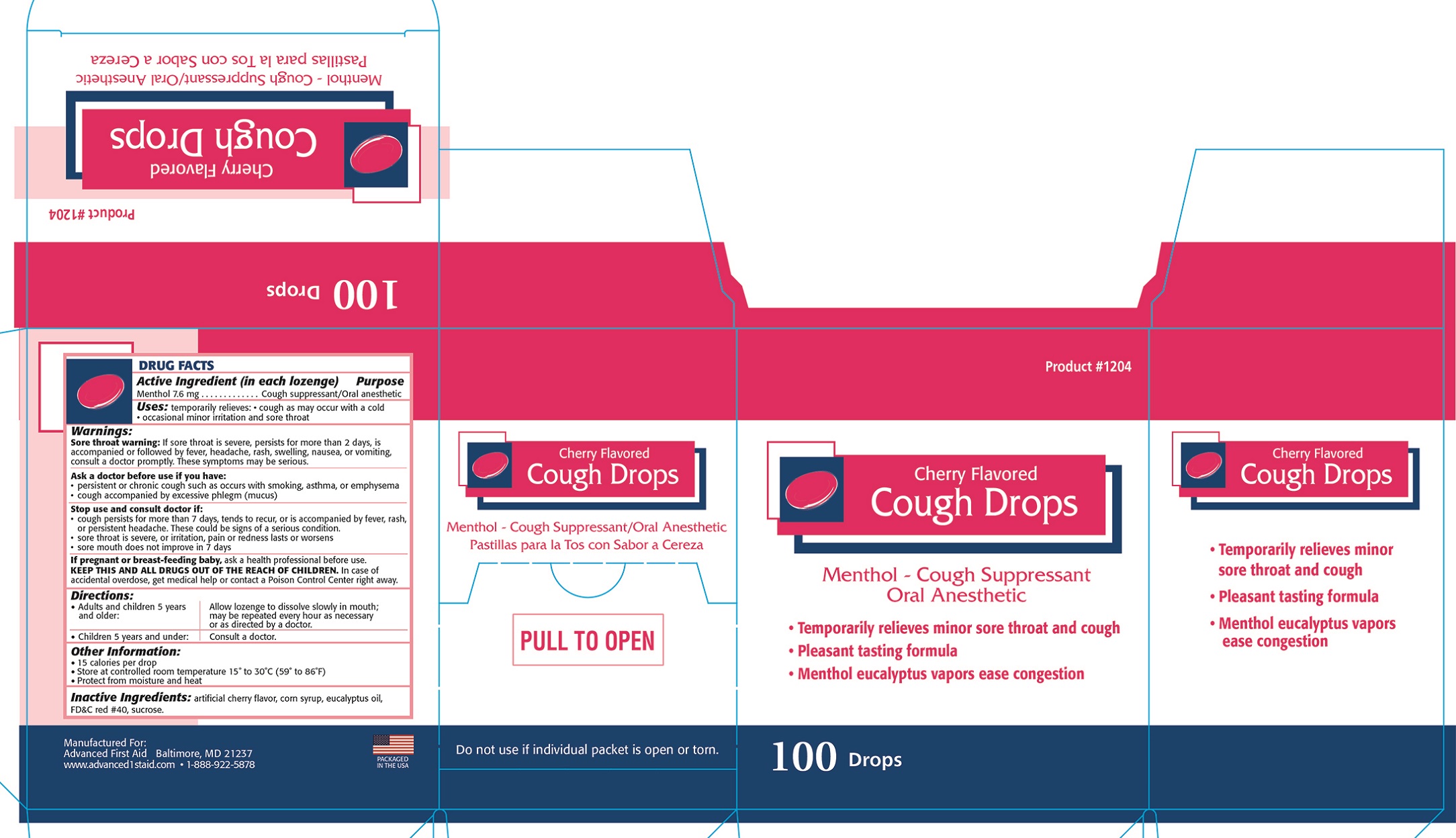 DRUG LABEL: ADVANCED CHERRY FLAVORED COUGH DROPS
NDC: 67060-120 | Form: LOZENGE
Manufacturer: ADVANCED FIRST AID, INC.
Category: otc | Type: HUMAN OTC DRUG LABEL
Date: 20190806

ACTIVE INGREDIENTS: MENTHOL 7.6 1/1 1
INACTIVE INGREDIENTS: SUCROSE; CORN SYRUP; EUCALYPTUS OIL; FD&C RED NO. 40

Active Ingredient (in each lozenge) - Menthol 7.6mg

PURPOSE

Cough suppressant / Oral anesthetic

INDICATIONS AND USAGE

Uses: temporarily relieves • cough as may occur with a cold • occaional minor irritation and sore throat

Warnings:

Sore throat warning: If sore throat is severe, persists for more than 2 days, is accompanied or followed by fever, headache, rash, swelling nausea, or vomiting, consult a doctor promptly. These symptoms may be serious.

Ask a doctor before use if you have: • persistent or chronic cough such as ocurs with smoking, asthma, or emphysema

• cough accompanied by excessive phlegm (mucus)

Stop use and consult a doctor if: • cough persists for more than 7 days, tends to recur, or is accompanied by fever, rash or persistent headache. These could be signs of a serious condition.

• sore throat is severe, or irritation, pain or redness lasts or worsens

• sore mouth does not improve in 7 days

PREGNANCY OR BREAST FEEDING

If pregnant or breast-feeding baby, ask a health professional before use.

KEEP OUT OF REACH OF CHILDREN

KEEP THIS AND ALL DRUGS OUT OF REACH OF CHILDREN. In case of accidental overdose, get medical help or contact a Poison Control Center right away.

Directions:

• Adults and children 5 years and over: Allow lozenge to dissolve slowly in mouth; may be repeated every hour as necessary or as directed by a doctor.

• Children under 5 years: Consult a doctor.

INACTIVE INGREDIENT

artificial cherry flavor, corn syrup, eucalyptus oil, FD& C red #40, sucrose